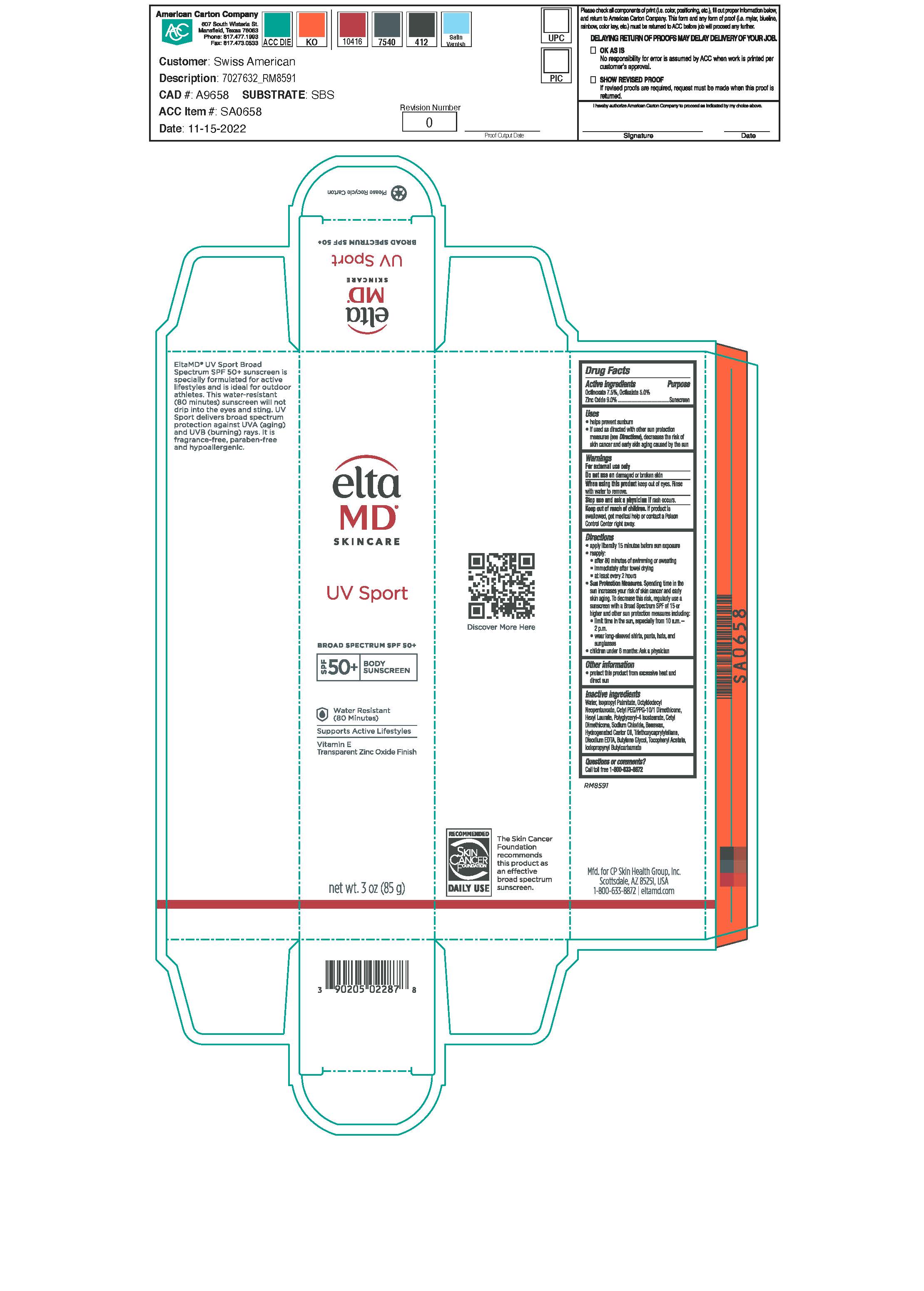 DRUG LABEL: EltaMD UV Sport SPF50
NDC: 72043-2287 | Form: LOTION
Manufacturer: CP Skin Health Group, Inc.
Category: otc | Type: HUMAN OTC DRUG LABEL
Date: 20240530

ACTIVE INGREDIENTS: ZINC OXIDE 90 g/1000 g; OCTINOXATE 75 g/1000 g; octisalate 50 g/1000 g
INACTIVE INGREDIENTS: WATER; EDETATE DISODIUM; SODIUM CHLORIDE; BUTYLENE GLYCOL; IODOPROPYNYL BUTYLCARBAMATE; ISOPROPYL PALMITATE; OCTYLDODECYL NEOPENTANOATE; CETYL DIMETHICONE 150; YELLOW WAX; HYDROGENATED CASTOR OIL; TRIETHOXYCAPRYLYLSILANE; .ALPHA.-TOCOPHEROL ACETATE, DL-; CETYL PEG/PPG-10/1 DIMETHICONE (HLB 1.5); POLYGLYCERYL-4 ISOSTEARATE; HEXYL LAURATE

EltaMD UV Sport SPF50

Warnings

For external use only Do not use on damaged or broken skin When suing this product keep out of eyes. Rinse with water to remove. Stop use and ask physician if rash occurs Keep out of reach of children. If product is swallowed contact a Poison Control Center right away.

Active ingredients

Zinc Oxide 9.0% Sunscreen
Octinoxate 7.5% Sunscreen
Octisalate 5.0% Sunscreen

Uses

Helps prevent sunburn If used as directed withother sun protection measures (See Directions) decreases the risk of skin cancer and early skin aging caued by the sun.

Directions

Apply liberally 15 minutes before sun exposure Reapply after 80 minutes of swimming or sweating immedaitely after towel drying at least every 2 hours Sun Protection Measures. Spending time in the sun increases your risk of skin cancer and early skin aging. To decrease this risk, regularly use a sunscreen with a broad spectrum SPF of 15 or higher and other sun protection measures including: limit time in the sun, especially from 10a.m.-2p.m. wear long-sleeve shirts, pants, hats and sunglasses Children under 6 months: Ask a physician

Doseage and administration

Apply liberally 15 minutes before sun exposure Reapply after 80 minutes of swimming or sweating immedaitely after towel drying at least every 2 hours

Inactive ingredients

Beeswax, Butylene Glycol, Cetyl Dimethicone, Cetyl PEG/PPG-10/ 1 Dimethicone, Disodium EDTA, Hexyl Laurate, Hydrogenated Castor Oil, Iodopropynyl Butylcarbamate, Isopropyl Palmitate, Octyldoceyl Neopentaoate, Polyglyceryl-4 Isostearate, Purified Water, Sodium Chloride, Tocopheryl Acetate, Triethoxycaprylylsilane

Keep out of reach of children